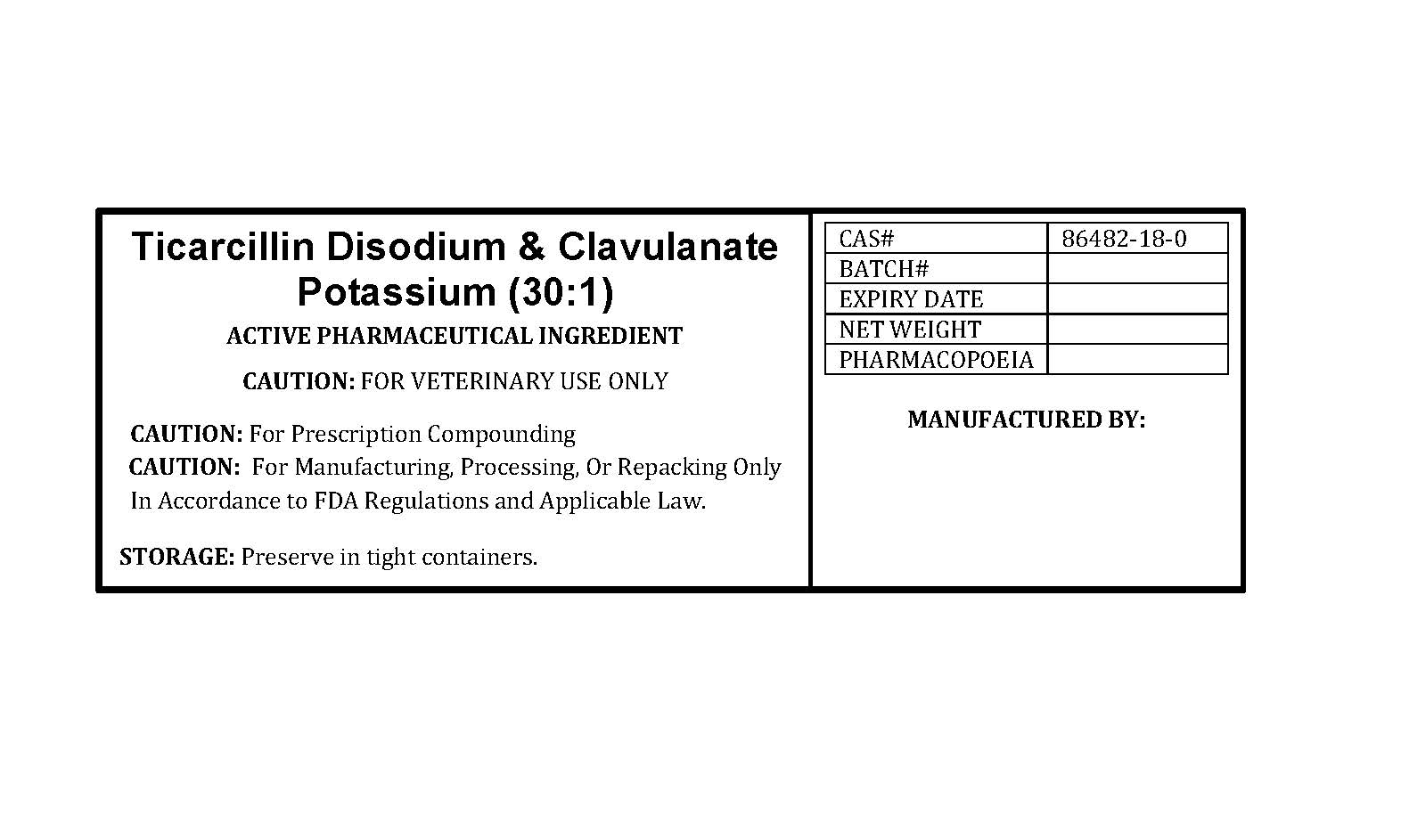 DRUG LABEL: TICARCILLIN DISODIUM AND CLAVULANATE POTASSIUM
NDC: 86184-385 | Form: POWDER
Manufacturer: MAEDA INC
Category: other | Type: BULK INGREDIENT - ANIMAL DRUG
Date: 20250821

ACTIVE INGREDIENTS: TICARCILLIN DISODIUM 968 mg/1 g; CLAVULANATE POTASSIUM 32 mg/1 g

TICARCILLIN DISODIUM AND CLAVULANATE POTASSIUM

PACKAGE LABEL

ticarcillinlabelfile.jpg